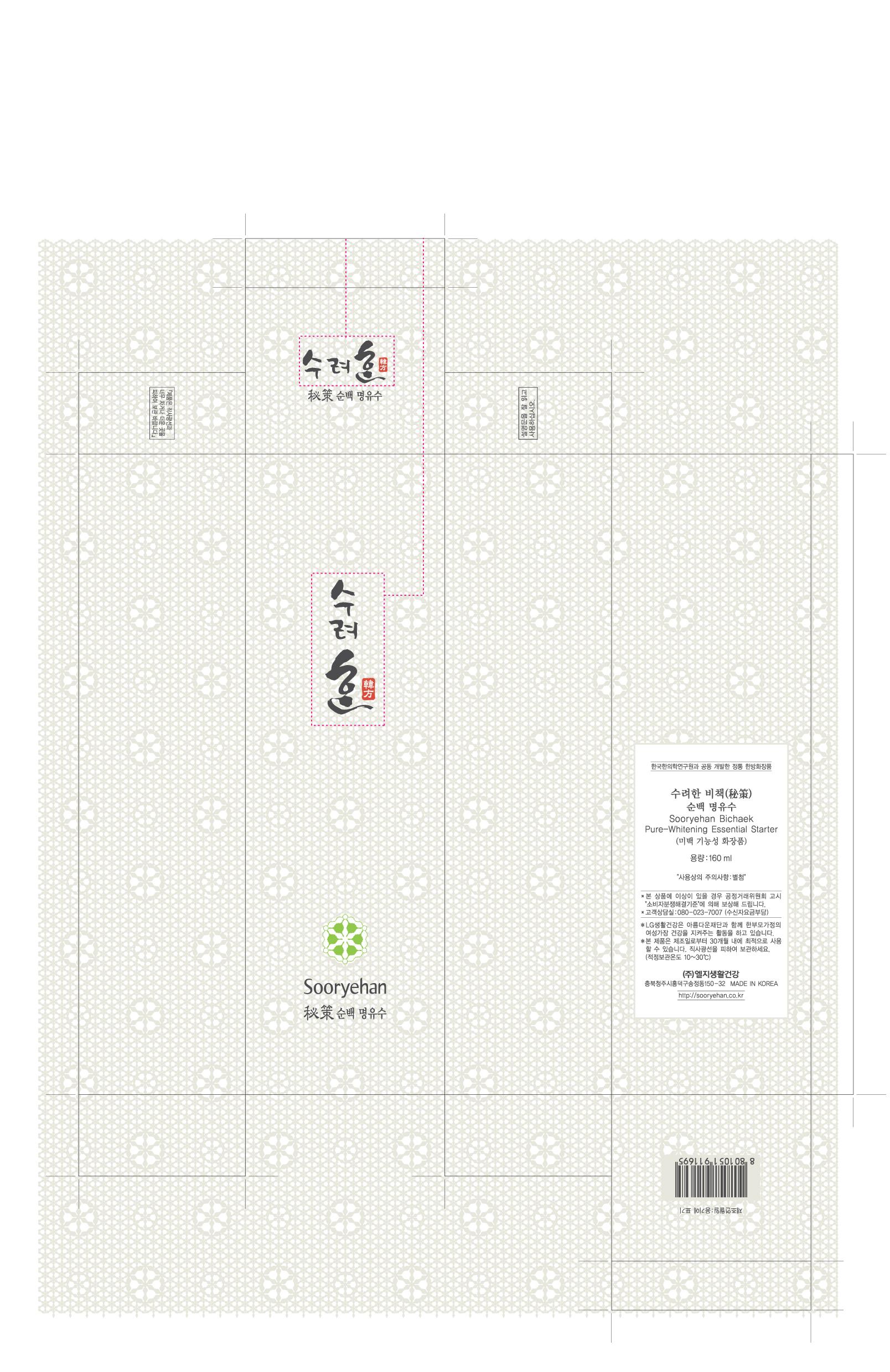 DRUG LABEL: Sooryehan Pure-Whitening Essential Starter
NDC: 53208-445 | Form: CREAM
Manufacturer: LG Household and Healthcare, Inc.
Category: otc | Type: HUMAN OTC DRUG LABEL
Date: 20100513

ACTIVE INGREDIENTS: ARBUTIN 2.1 mL/100 mL
INACTIVE INGREDIENTS: WATER; DIPROPYLENE GLYCOL; GLYCERIN; CETOSTEARYL ALCOHOL; TROLAMINE; FD&C YELLOW NO. 5; FD&C YELLOW NO. 6

DRUG FACTS

ACTIVE INGREDIENT

ARBUTIN 2.1mL/100mL

WARNINGS AND PRECAUTIONS

For external use only

Keep out of reach of children. Is swallowed, get medical help or contact a Poison Control Center right away.

WHEN USING

Keep out of eyes. Rinse with water to remove.

Stop use if a rash or irritation develops and lasts.

PACKAGE LABEL

Sooryehan